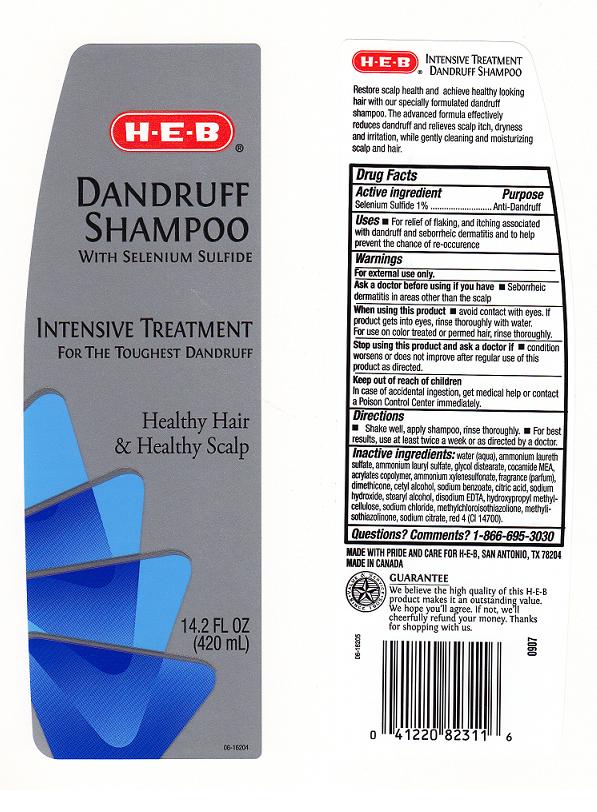 DRUG LABEL: HEB Dandruff 
NDC: 37808-613 | Form: SHAMPOO
Manufacturer: H E B
Category: otc | Type: HUMAN OTC DRUG LABEL
Date: 20110805

ACTIVE INGREDIENTS: SELENIUM SULFIDE 1 mL/100 mL
INACTIVE INGREDIENTS: WATER; AMMONIUM LAURETH-2 SULFATE; AMMONIUM LAURYL SULFATE; GLYCOL DISTEARATE; COCO MONOETHANOLAMIDE; CARBOMER 934; 3-HYDROXY-4-METHOXYBENZENESULFONIC ACID; DIMETHICONE; CETYL ALCOHOL; SODIUM BENZOATE; CITRIC ACID MONOHYDRATE; SODIUM HYDROXIDE; STEARYL ALCOHOL; EDETATE DISODIUM; HYPROMELLOSES; SODIUM CHLORIDE; METHYLCHLOROISOTHIAZOLINONE; METHYLISOTHIAZOLINONE; SODIUM CITRATE; FD&C RED NO. 4

DRUG FACTS

ACTIVE INGREDIENT

SELENIUM SULFIDE ONE PERCENT

PURPOSE

ANTI DANDRUFF

USES

For relief of flaking, and itching associated with dandruff and seborrheic dermatitis and to help prevent the chance of reoccurence

WARNINGS

FOR EXTERNAL USE ONLY.

ASK A DOCTOR BEFORE USING IF YOU HAVE

SEBORRHEIC DERMATITIS IN AREAS OTHER THAN THE SCALP.

WHEN USING THIS PRODUCT

AVOID CONTACT WITH EYES. IF PRODUCT GETS INTO EYES, RINSE THOROUGHLY WITH WATER. FOR USE ON COLOR TREATED OR PERMED HAIR, RINSE THOROUGHLY.

STOP USING THIS PRODUCT AND ASK A DOCTOR IF

CONDITION WORSENS OR DOES NOT IMPROVE AFTER REGULAR USE OF THIS PRODUCT AS DIRECTED.

KEEP OUT OF REACH OF CHILDREN

IN CASE OF ACCIDENTAL INGESTION, GET MEDICAL HELP OR CONTACT A POISON CONTROL CENTER IMMEDIATELY.

DIRECTIONS

SHAKE WELL, APPLY A SHAMPOO, RINSE THOROUGHLY. FOR BEST RESULTS, USE AT LEAST TWICE A WEEK OR AS DIRECTED BY A DOCTOR.

INACTIVE INGREDIENTS

WATER, AMMONIUM LAURETH SULFATE, AMMONIUM LAURYL SULFATE, GLYCOL DISTEARATE, COCAMIDE MEA, ACRYLATES COPOLYMER, AMMONIUM XYLENESULFONATE, FRAGRANCE, DIMETHICONE, CETYL ALCOHOL, SODIUM BENZOATE, CITRIC ACID, SODIUM HYDROXIDE, STEARYL ALCOHOL, DISODIUM EDTA, HYDROXYPROPYL METHYLCELLULOSE, SODIUM CHLORIDE, METHYLCHLOROISOTHIAZOLINONE, METHYLISOTHIAZOLINONE, SODIUM CITRATE, RED 4 (CI 14700).